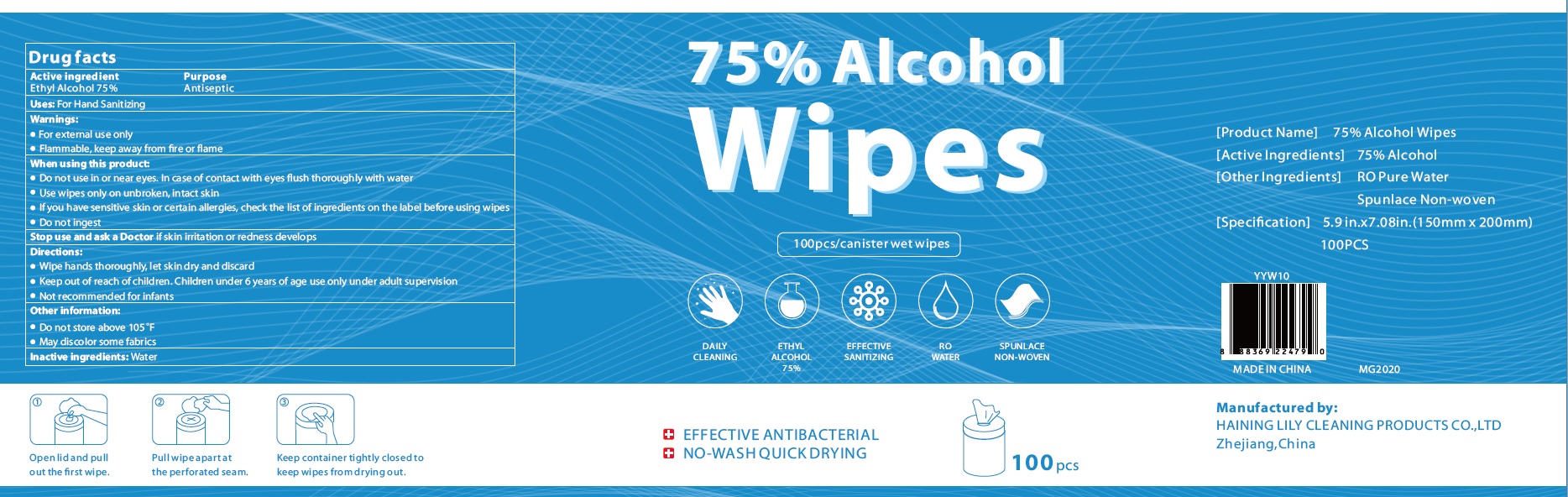 DRUG LABEL: Alcohol Wipes
NDC: 77435-012 | Form: SWAB
Manufacturer: HAINING LILY CLEANING PRODUCTS CO., LTD
Category: otc | Type: HUMAN OTC DRUG LABEL
Date: 20200712

ACTIVE INGREDIENTS: ALCOHOL 75 g/100 g
INACTIVE INGREDIENTS: water

alcohol Wipes

Active Ingredient

Ethyl Alcohol 75%

Purpose

Antiseptic

USE

For hand sanitizing

Warning

- Flammable, keep away from fire or flame.
- For external use only.

When using this product,

- Do not use in or near the eyes. In case of contact, flush eyes thoroughly with water.
- Use wipes only on unbroken, intact skin.
- If you have sensitive skin or certain allergies, chck the list of ingedients on the label before using wipes.
- Do not ingest.

Stop use and ask a Doctor if skin irritation or redness develops.

Other Informtion:

- Do not store above 105℉
- May discolor some fabrics

KEEP OUT OF REACH OF CHILDREN

Children under 6 years of age use only under adult supervision.

Directions

- Wipe hands thoroughly, let skin dry and discard
- Not recommended for infants.

Inactive ingredients

water